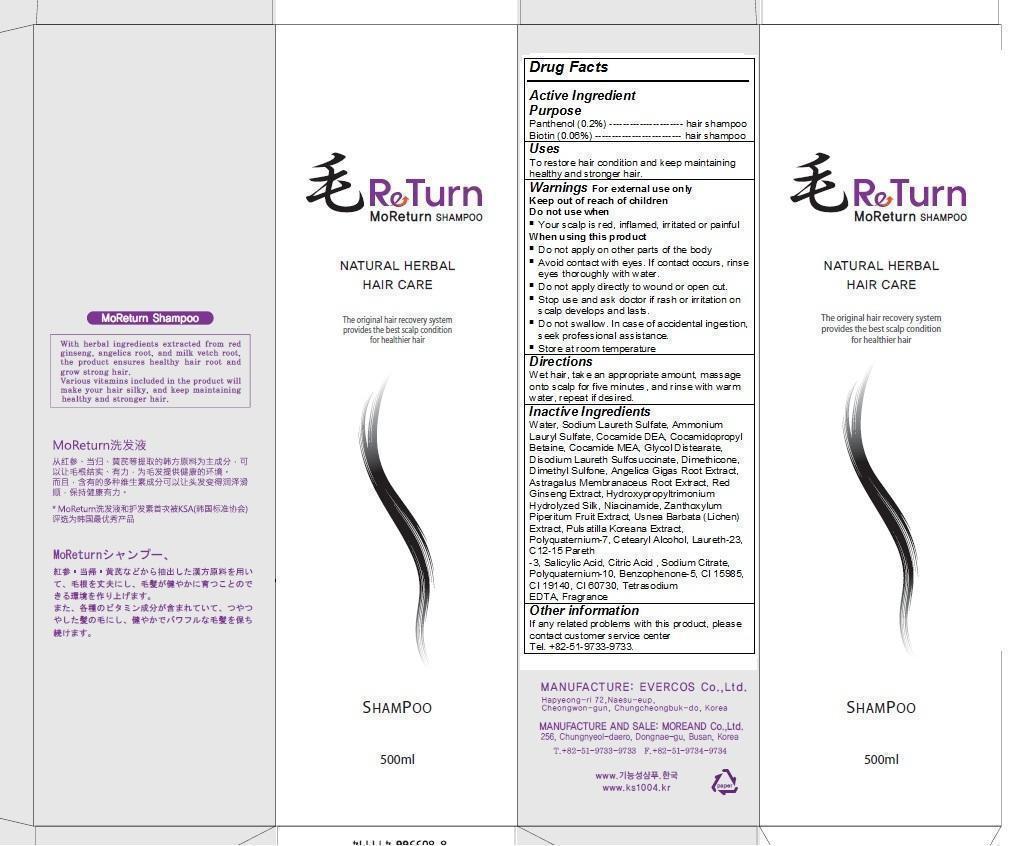 DRUG LABEL: MoReturn Hair
NDC: 61310-102 | Form: SHAMPOO
Manufacturer: Moreand Co., Ltd.
Category: otc | Type: HUMAN OTC DRUG LABEL
Date: 20140206

ACTIVE INGREDIENTS: PANTHENOL 1.0 g/500 mL; BIOTIN 0.3 g/500 mL
INACTIVE INGREDIENTS: water; SODIUM LAURETH SULFATE; AMMONIUM LAURYL SULFATE; COCO DIETHANOLAMIDE; COCAMIDOPROPYL BETAINE; GLYCOL DISTEARATE; DISODIUM LAURETH SULFOSUCCINATE; DIMETHICONE; DIMETHYL SULFONE; ANGELICA GIGAS ROOT; ASTRAGALUS PROPINQUUS ROOT; ASIAN GINSENG; NIACINAMIDE; ZANTHOXYLUM PIPERITUM FRUIT PULP; USNEA BARBATA; PULSATILLA KOREANA WHOLE; POLYQUATERNIUM-7 (70/30 ACRYLAMIDE/DADMAC; 1600 KD); CETOSTEARYL ALCOHOL; LAURETH-23; C12-15 PARETH-3; SALICYLIC ACID; CITRIC ACID ACETATE

MoReturn hair

For external use only

Do not use when Your scalp is red, inflamed, irritated or painful.

Do not apply on other parts of the body.

Avoid contact with eyes. If contact occurs, rinse eyes thoroughly with water.

Do not apply directly to wound or open cut.

Stop use and ask doctor if rash or irritation on scalp develops and lasts.

Do not swallow. In case of accidental ingestion, seek professional assistance.

Store at room temperature

MoReturn Shampoo

NATURAL HERBAL HAIR CARE The original hair recovery system provides the best scalp condition for healthier hair. With herbal ingredients extracted from red ginseng, angelica root, and milk vetch root, the product ensures healthy hair root and grow strong hair. Various vitamins included in the product will make your hair silky, and keep maintaining healthy and stronger hair.